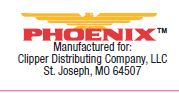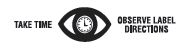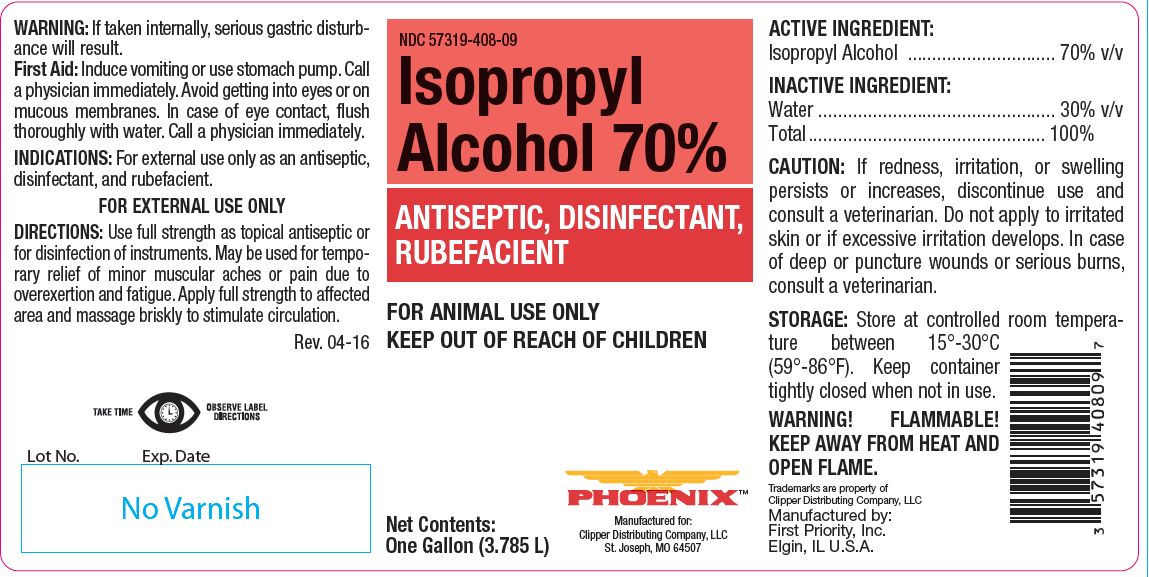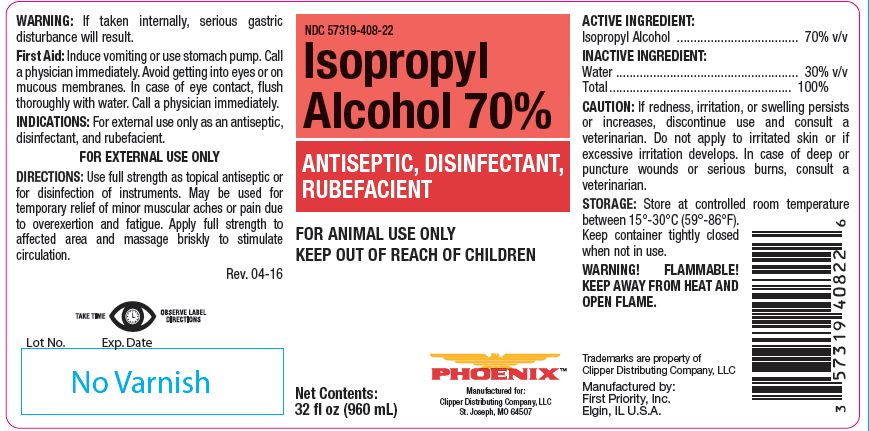 DRUG LABEL: Isopropyl Alcohol
NDC: 57319-408 | Form: SOLUTION
Manufacturer: Clipper Distributing Company, LLC
Category: animal | Type: OTC ANIMAL DRUG LABEL
Date: 20241029

ACTIVE INGREDIENTS: ISOPROPYL ALCOHOL 557.25 g/1 L

Isopropyl Alcohol 70%

PURPOSE

ANTISEPTIC, DISINFECTANT, RUBEFACIENT

KEEP OUT OF REACH OF CHILDREN

FOR ANIMAL USE ONLY
KEEP OUT OF REACH OF CHILDREN

WARNING:

If taken internally, serious gastric disturbance will result.

First Aid:

Induce vomiting or use stomach pump. Call a physician immediately. Avoid getting into eyes or on mucous membranes. In case of eye contact, flush thoroughly with water. Call a physician immediately.

INDICATIONS:

For external use only as an antiseptic, disinfectant, and rubefacient.
FOR EXTERNAL USE ONLY

DIRECTIONS:

Use full strength as topical antiseptic or for disinfection of instruments. May be used for temporary relief of minor muscular aches or pain due to overexertion and fatigue. Apply full strength to affected area and massage briskly to stimulate circulation.

ACTIVE INGREDIENT:

Isopropyl Alcohol .............................. 70% v/v

INACTIVE INGREDIENT:

Water ................................................ 30% v/v
Total ................................................ 100%

CAUTION:

If redness, irritation, or swelling persists or increases, discontinue use and consult a veterinarian. Do not apply to irritated skin or if excessive irritation develops. In case of deep or puncture wounds or serious burns, consult a veterinarian.

STORAGE:

Store at controlled room temperature between 15°-30°C (59°-86°F). Keep container tightly closed when not in use.
WARNING! FLAMMABLE! KEEP AWAY FROM HEAT AND OPEN FLAME.

Net Contents:

32 fl oz (960 mL)

One Gallon (3.785 L)

INFORMATION FOR OWNERS/CAREGIVERS

Trademarks are property of Clipper Distributing Company, LLC

Manufactured by:
First Priority, Inc.
Elgin, IL U.S.A.